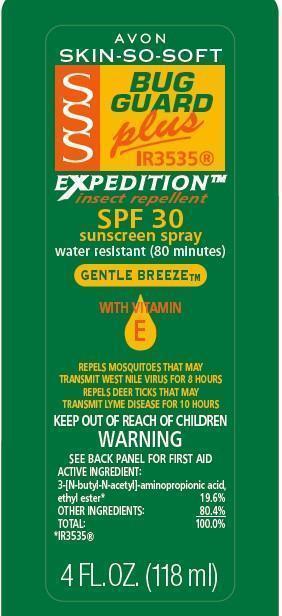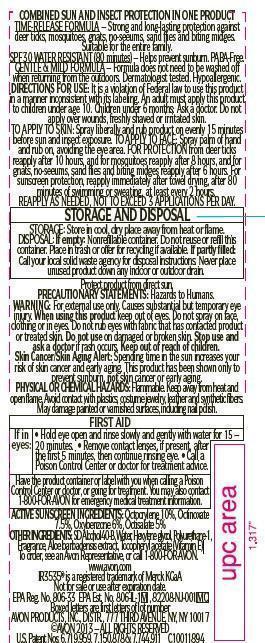 DRUG LABEL: Skin So Soft Bug Guard Plus IR3535
NDC: 10096-0121 | Form: SPRAY
Manufacturer: New Avon LLC
Category: otc | Type: HUMAN OTC DRUG LABEL
Date: 20190101

ACTIVE INGREDIENTS: OCTOCRYLENE 100 mg/1 mL; OCTINOXATE 75 mg/1 mL; OXYBENZONE 60 mg/1 mL; OCTISALATE 50 mg/1 mL
INACTIVE INGREDIENTS: WATER

SSS BG+ Expedition SPF 30 Pump Spray

INDICATIONS AND USAGE

Helps prevent sunburn.

DOSAGE AND ADMINISTRATION

DIRECTIONS FOR USE: It is a violation of Federal law to use this product in a manner inconsistent with its labeling. An adult must apply this product to children under age 10. Children under 6 months: Ask a doctor. Do not apply over wounds, freshly shaved or irritated skin.
TO APPLY TO SKIN: Spray liberally and rub product on evenly 15 minutes before sun and insect exposure. TO APPLY TO FACE: Spray palm of hand and rub on, avoiding the eye area. FOR PROTECTION from deer ticks reapply after 10 hours, and for mosquitoes reapply after 8 hours, and for gnats, no-seeums, sand flies and biting midges reapply after 6 hours. For sunscreen protection, reapply immediately after towel drying, after 80 minutes of swimming or sweating, at least every 2 hours. REAPPLY AS NEEDED, NOT TO EXCEED 3 APPLICATIONS PER DAY.

STORAGE AND HANDLING

STORAGE: Store in cool, dry place away from heat or flame.

Protect product from direct sun.

WARNINGS

WARNING: For external use only. Causes substantial but temporary eye injury. When using this product keep out of eyes. Do not spray on face, clothing or in eyes. Do not rub eyes with fabric that has contacted product or treated skin. Do not use on damaged or broken skin. Stop use and ask a doctor if rash occurs. Keep out of reach of children. Skin Cancer/Skin Aging Alert: Spending time in the sun increases your risk of skin cancer and early aging. This product has been shown only to prevent sunburn, not skin cancer or early aging.

ACTIVE INGREDIENT

ACTIVE SUNSCREEN INGREDIENTS: Octocrylene 10%, Octinoxate 7.5%, Oxybenzone 6%, Octisalate 5%

INACTIVE INGREDIENT

OTHER INGREDIENTS: SD Alcohol 40-B, Water, Hexylene glycol, Polyurethane-1, Fragrance, Aloe barbadensis extract, Tocopheryl acetate (Vitamin E)